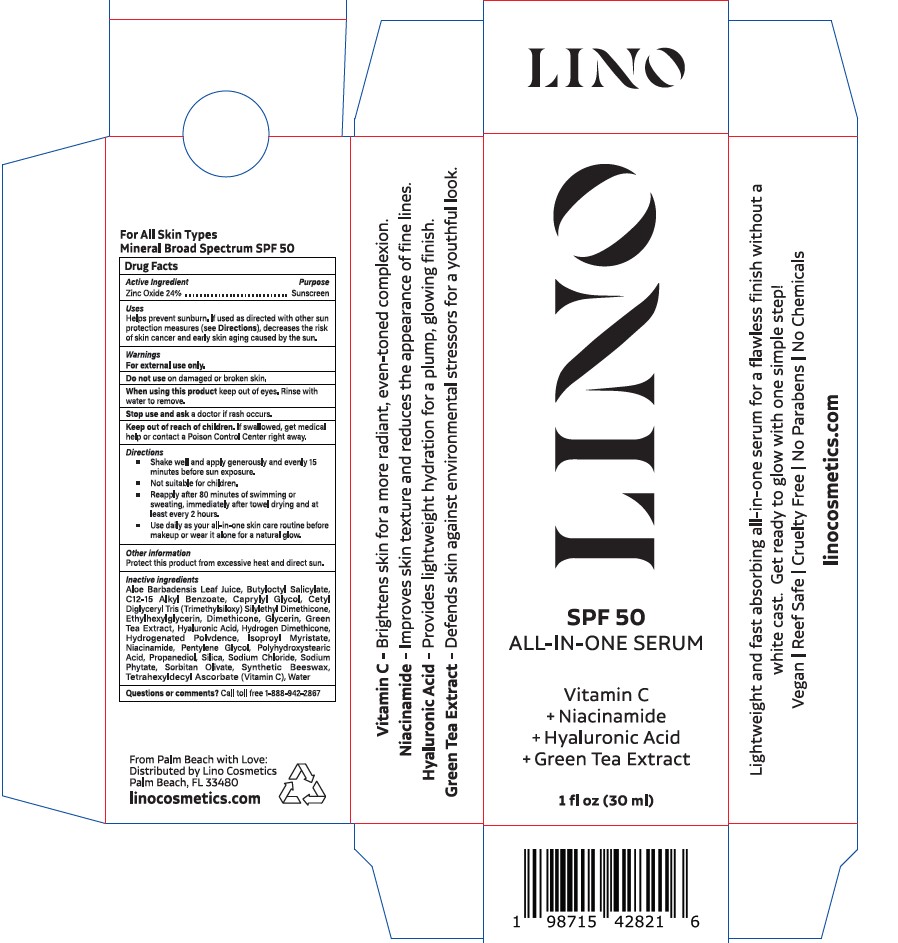 DRUG LABEL: LINO
NDC: 84749-001 | Form: CREAM
Manufacturer: Lino Cosmetics LLC
Category: otc | Type: HUMAN OTC DRUG LABEL
Date: 20260112

ACTIVE INGREDIENTS: ZINC OXIDE 24 g/100 g
INACTIVE INGREDIENTS: BUTYLOCTYL SALICYLATE; GLYCERIN; NIACINAMIDE; SODIUM CHLORIDE; SODIUM PHYTATE; GREEN TEA LEAF; ALOE VERA LEAF; CAPRYLYL GLYCOL; ETHYLHEXYLGLYCERIN; ASCORBYL TETRAISOPALMITATE; PHENOXYETHANOL; SILICA; SORBITAN OLIVATE; C13-15 ALKANE; CETYL DIGLYCERYL TRIS(TRIMETHYLSILOXY)SILYLETHYL DIMETHICONE (950 MM2/S); WATER; DIMETHICONE; ISOPROPYL MYRISTATE; PROPANEDIOL; SYNTHETIC BEESWAX; PENTYLENE GLYCOL

LINO SPF 50 ALL-IN-ONE SERUM

Active Ingredient

Zinc Oxide 24.00%

Purpose

Sunscreen

Uses

Helps prevent sunburn. If used as directed with other sun protection measures (see Directions), decreases the risk of skin cancer and early skin aging caused by the sun.

Warnings

For external use only.

Do not use on damaged or broken skin.

When using this product keep out of eyes. Rinse with water to remove.

Stop use

Stop use and ask a doctor if rash occurs.

Keep out of reach of children If swallowed, get medical help or contact a Poison Control Center right away.

Direction

Directions

Apply generously and evenly 15 minutes before sun exposure

Not suitable for children
apply to all skin exposed to the sun

Reapply

after 80 minutes of swimming or sweating
immediately after towel drying
at least every 2 hours

Apply using your hands, blending into the top half of your arm, then forearm, upper leg and then lower leg, ensuring you are covering all skin. Use more product if needed.

This product includes a gradual tan, therefore, please wash hands after use as product may stain.

Inactive Ingredients

Aloe Barbadensis Leaf

Ascorbyl Tetraisopalmitate

Butyloctyl Salicylate

C13-15 Alkane

Caprylyl Glycol

Cetyl Diglyceryl Tris(Trimethylsiloxy)silylethyl Dimethicone

Dimethicone

Ethylhexylglycerin

Glycerin

Green Tea Extract

Isopropyl Myristate

Niacinamide

Pentylene Glycol

Phenoxyethanol

Polyhydroxystearic acid

Propanediol

Silica

Sodium Chloride

Sodium Phytate

Sorbitan Olivate

Synthetic Beeswax

Water

Questions?

Call toll free 1-888-942-2887